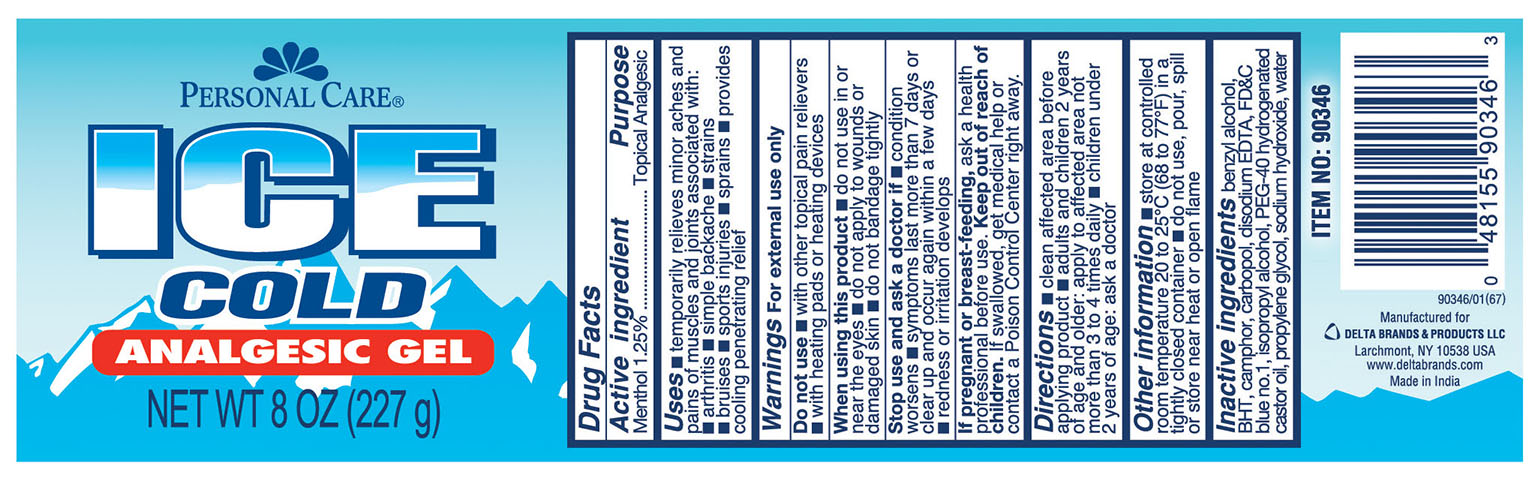 DRUG LABEL: Ice Gel
NDC: 30400-110 | Form: GEL
Manufacturer: Jell Pharmaceuticals Pvt Ltd
Category: otc | Type: HUMAN OTC DRUG LABEL
Date: 20260211

ACTIVE INGREDIENTS: MENTHOL 1.25 g/100 g
INACTIVE INGREDIENTS: PROPYLENE GLYCOL; BENZYL ALCOHOL; BUTYLATED HYDROXYTOLUENE; CARBOXYPOLYMETHYLENE; EDETATE DISODIUM; FD&C BLUE NO. 1; ISOPROPYL ALCOHOL; POLYOXYL 40 HYDROGENATED CASTOR OIL; SODIUM HYDROXIDE; WATER; CAMPHOR (SYNTHETIC)

Ice Gel

Active ingredient

Menthol 1.25%

Purpose

Topical Analgesic

Uses

■ temporarily relieves minoraches and pains of muscles and joints associated with:

■ arthritis ■ simple backache ■ strains ■ bruises ■ sports injuries ■ sprains ■ provides cooling penetrating relief

Warnings

For external use only

Do not use

■ with other topical relievers ■ with heating pads or heating devices

When using this product

■ do not use in or near the eyes ■ do not apply to wounds or damaged skin ■ do not bandage tightly

Stop use and ask a doctor if

■ condition worsens ■ symptoms last more than 7 days or clear up and occur again within a few days ■ redness or irritation develops

Keep out of reach of children

If pregnant or breast-feeding,ask a health professional before use. If swallowed, get medical help or contact a Poison Control Center right away.

Directions

■ clean affected area before applying product ■ adults and children 2 years of age and older: apply to affected area not more than 3 to 4 times daily ■ children under 2 years of age: ask a doctor

Other information

■ stroe at controlled room temperature 20 to 25 ºC (68 to 77ºF) in a tightly closed container ■ do not use, pour, spill or store near heat or open flame

Inactive Ingredients

benzyl alcohol, BHT, camphor, carbopol, disodium EDTA, FD&C blue no. 1, isopropyl alcohol, PEG-40 hydrogenated castor oi, propylene glycol, sodium hydroxide, water